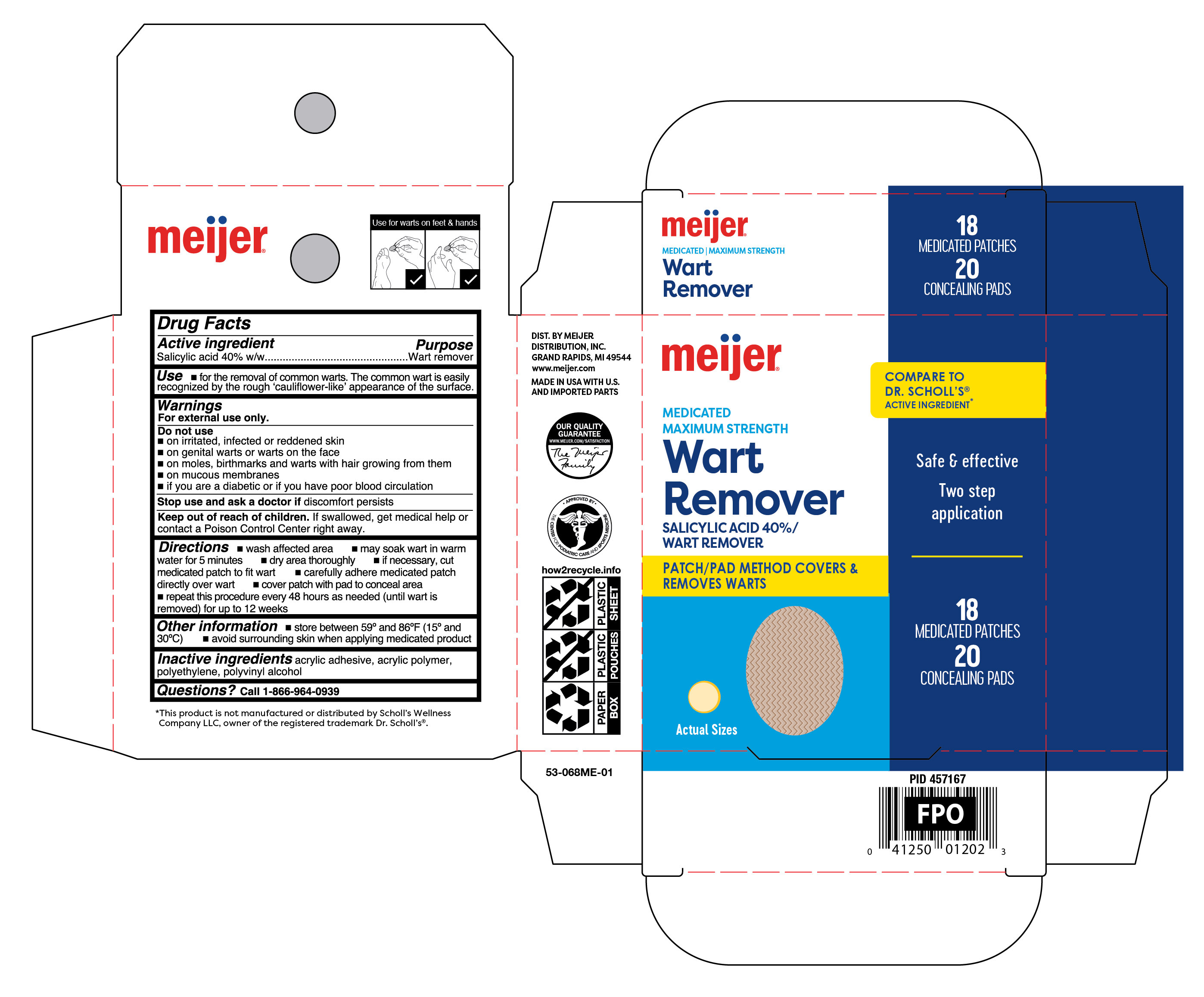 DRUG LABEL: Wart Removers
NDC: 79481-0620 | Form: PATCH
Manufacturer: Meijer Distribution Inc
Category: otc | Type: HUMAN OTC DRUG LABEL
Date: 20260115

ACTIVE INGREDIENTS: SALICYLIC ACID 400 mg/1 g
INACTIVE INGREDIENTS: POLYVINYL ALCOHOL, UNSPECIFIED; HIGH DENSITY POLYETHYLENE

Meijer Medicated Wart Removers

Active ingredient

Salicylic acid 40% w/w

Purpose

Wart remover

Use

for the removal of common warts. The common wart is easily recognized by the rough 'cauliflower-like' appearance of the surface.

Warnings

For external use only.

Do not use

- on irritated, infected or reddened skin
- on general warts and warts on the face
- on moles, birthmarks and warts with hair growing from them
- on mucous membranes
- if you are a diabeticor if you have poor blood circulation

Stop use and ask a doctor if

discomfort persists

Keep out of reach of children.

If swallowed, get medical help or contact a Poison Control Center right away.

Directions

- wash affected area
- may soak wart in warm water for 5 minutes
- dry area thoroughly
- if necessary, cut medicated patch to fit wart
- carefully adhere medicated patch directly over wart
- cover patch with pad to conceal area
- repeat this procedure every 48 hours as needed (until wart is removed) for up to 12 weeks

Other information

- store between 59°F to 86°F (15°C to 30°C)
- avoid surrounding skin when applying medicated product

Inactive ingredients

acrylic adhesive, acrylic polymer, polyethylene, polyvinyl alcohol

Questions?

Call 1-866-964-0939

Principal Display Panel

meijer

MEDICATED

MAXIMUM STRENGTH

Wart

Remover

Salicylic Acid 40%/Wart Remover

Two-Step Application

Patch/pad method covers & removes warts

Maximum Strength

Safe & effective

18 Medicated Patches

20 Concealing Pads